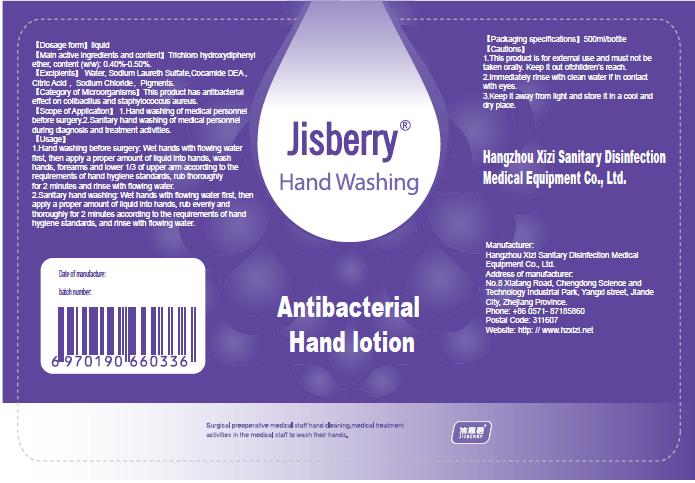 DRUG LABEL: Jisberry Antibacterial Handlotion
NDC: 52738-005 | Form: LOTION
Manufacturer: Hangzhou Xizi Sanitary Disinfection Medical Equipment Co., Ltd
Category: otc | Type: HUMAN OTC DRUG LABEL
Date: 20200426

ACTIVE INGREDIENTS: TRICLOSAN 2 g/500 mL
INACTIVE INGREDIENTS: WATER; SODIUM LAURETH SULFATE; CITRIC ACID MONOHYDRATE; SODIUM CHLORIDE; CHLOROPHYLL; COCO DIETHANOLAMIDE

DOSAGE AND ADMINISTRATION

Keep it away from Iight and store tina cool and dry place.

INACTIVE INGREDIENT

Water

Sodium Laureth Sulfate

Cocamide DEA

Citric Acid

Sodium Chloride

Pigments

INDICATIONS AND USAGE

1.Hand washing before surgery: Wet hands with flowing water first, then apply a proper amount of liquid into hands, wash hands, forearms and lower 1/3 of upper arm according to the requirements of hand hygiene standards, rub thoroughly for 2 minutes and rinse with flowing water.
2.Sanitary hand washing: Wet hands with flowing water first, then apply a proper amount of liquid into hands, rub evenly and thoroughly for 2 minutes according to the requirements of hand hygiene standards, and rinse with flowing water.

ACTIVE INGREDIENT

Triclosan

keep out of children

PURPOSE

Disinfection
Sterilization

WARNINGS

1.This product is for external use and must not be taken orally. Keep it out ofchildren's reach.
2.Immediately rinse with clean water if in contact with eyes.
3.Keep it away from light and store it in a cool and dry place.